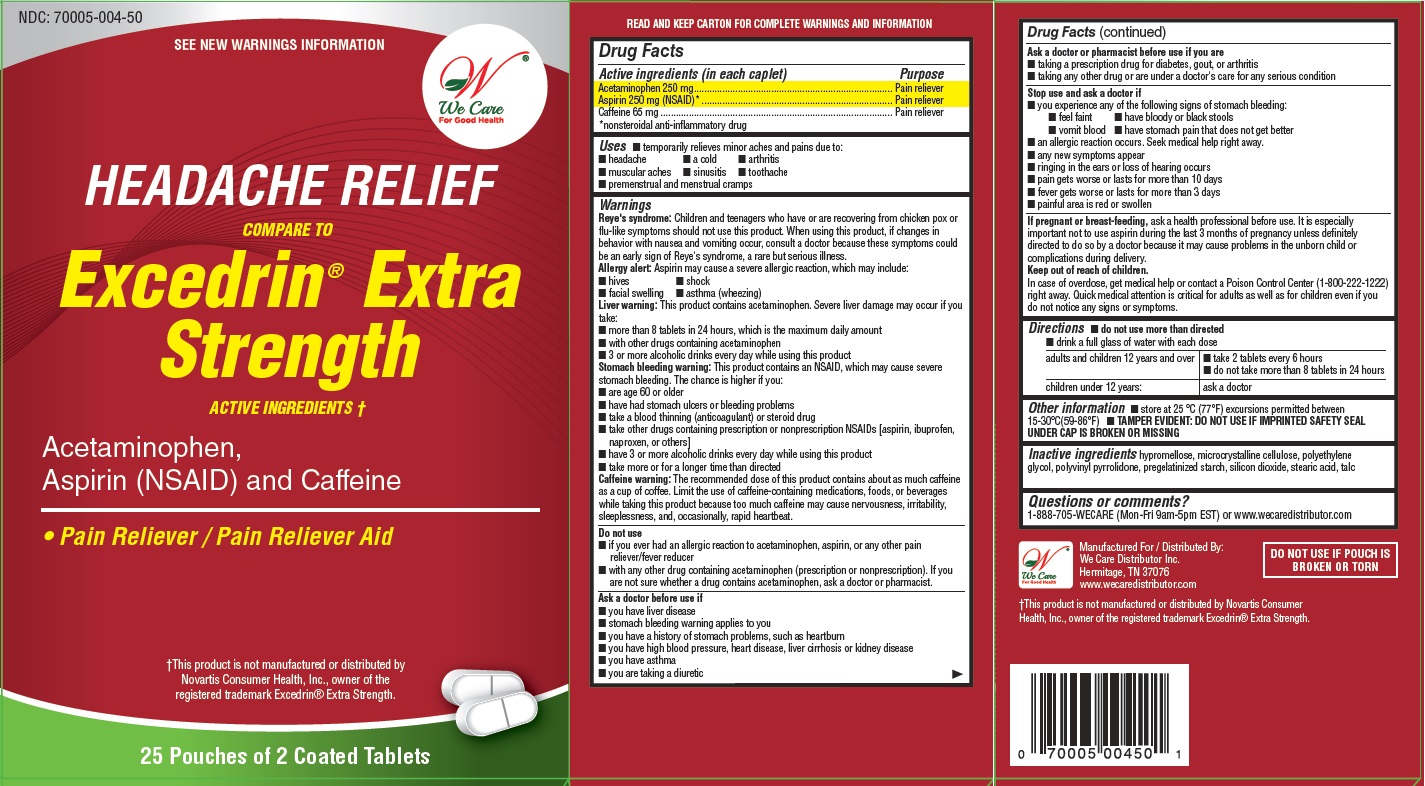 DRUG LABEL: Headache Relief
NDC: 70005-004 | Form: TABLET
Manufacturer: We Care Distributor Inc.
Category: otc | Type: HUMAN OTC DRUG LABEL
Date: 20160209

ACTIVE INGREDIENTS: Acetaminophen 250 mg/1 1; Aspirin 250 mg/1 1; Caffeine 65 mg/1 1
INACTIVE INGREDIENTS: HYPROMELLOSES; SILICON DIOXIDE; STARCH, PREGELATINIZED CORN; CELLULOSE, MICROCRYSTALLINE; POLYETHYLENE GLYCOL 400; STEARIC ACID; TITANIUM DIOXIDE; TALC

Headache Relief - Acetaminophen, Aspirin and Caffeine

Drug Facts

ACTIVE INGREDIENT

PURPOSE

Active ingredients (in each tablet) | Purposes
Acetaminophen 250 mg | Pain reliever
Aspirin 250 mg (NSAID) [nonsteroidal anti-inflammatory drug] | Pain reliever
Caffeine 65 mg | Pain reliever aid

Uses

- temporarily relieves minor aches and pains due to:
  - headache
  - a cold
  - arthritis
  - muscular aches
  - sinusitis
  - toothache
  - premenstrual & menstrual cramps

Warnings

Reye's syndrome

Children and teenagers who have or are recovering from chicken pox or flu-like symptoms should not use this product. When using this product, if changes in behavior with nausea and vomiting occur, consult a doctor because these symptoms could be an early sign of Reye's syndrome, a rare but serious illness.

Allergy alert

Aspirin may cause a severe allergic reaction which may include:

- hives
- facial swelling
- asthma (wheezing)
- shock

Liver warning

This product contains acetaminophen. Severe liver damage may occur if you take

- adult takes more than 8 tablets in 24 hours, which is the maximum daily amount
- child takes more than 5 tablets in 24 hours
- with other drugs containing acetaminophen
- 3 or more alcoholic drinks every day while using this product

Stomach bleeding warning

This product contains an NSAID, which may cause severe stomach bleeding. The chance is higher if you

- are age 60 or older
- have had stomach ulcers or bleeding problems
- take a blood thinning (anticoagulant) or steroid drug
- take other drugs containing prescription or nonprescription NSAIDs (aspirin, ibuprofen, naproxen, or others)
- have 3 or more alcoholic drinks every day while using this product
- take more or for a longer time than directed

Caffeine warning

The recommended dose of this product contains about as much caffeine as a cup of coffee. Limit the use of caffeine-containing medications, foods, or beverages while taking this product because too much caffeine may cause nervousness, irritability, sleeplessness, and, occasionally, rapid heart beat.

Do not use

- if you have ever had an allergic reaction to acetaminophen, aspirin or any other pain reliever/fever reducer
- with any other drug containing acetaminophen (prescription or nonprescription). If you are not sure whether a drug contains acetaminophen, ask a doctor or pharmacist.

Ask a doctor before use if

- you have liver disease
- stomach bleeding warning applies to you
- you have not been drinking fluids
- you have a history of stomach problems, such as heartburn
- you have high blood pressure, heart disease, liver cirrhosis, or kidney disease
- you are taking a diuretic
- you have asthma
- you have lost a lot of fluids due to vomiting or diarrhea

Ask a doctor or pharmacist before use if you are taking

- any other drug containing an NSAID (prescription or nonprescription)
- a blood thinning (anticoagulant) or steroid drug
- a prescription drug for diabetes, gout, or arthritis
- any other drug, or are under a doctor's care for any serious condition

Stop use and ask a doctor if

- an allergic reaction occurs. Seek medical help right away.
- you experience any of the following signs of stomach bleeding:
  - feel faint
  - vomit blood
  - have bloody or black stools
  - have stomach pain that does not get better
  - ringing in the ears or loss of hearing occurs
  - painful area is red or swollen
  - pain gets worse or lasts for more than 10 days
  - fever gets worse or lasts for more than 3 days
  - any new symptoms appear

PREGNANCY OR BREAST FEEDING

If pregnant or breast-feeding, ask a health professional before use. It is especially important not to use aspirin during the last 3 months of pregnancy unless definitely directed to do so by a doctor because it may cause problems in the unborn child or complications during delivery.

Keep out of reach of children.

In case of overdose, get medical help or contact a Poison Control Center (1-800-222-1222) right away. Quick medical attention is critical for adults as well as for children even if you do not notice any signs or symptoms.

Directions

- do not use more than directed
- drink a full glass of water with each dose
- adults and children 12 years and over: take 2 tablets every 6 hours; do not take more than 8 tablets in 24 hours
- children under 12 years: ask a doctor

Other information

- store at 25 °C (77°F) excursions permitted between 15-30°C(59-86°F)
- read all product information before using. Keep this box for important information

Inactive ingredients

hypromellose, microcrystalline cellulose, polyethylene glycol, polyvinyl pyrrolidone, pregelatinized starch, silicon dioxide, stearic acid, talc

Questions or comments?

1-888-705-WECARE (Mon-Fri 9am-5pm EST) or www.wecaredistributor.com

PRINCIPAL DISPLAY PANEL

See New Warnings Information & Directions

Compare to the Active Ingredients in
EXCERDRIN EXTRA STRENGTH

Acetaminophen, Asprin (NSAID) and Caffeine

TO OPEN
PUSH IN TAB AND PULL OUT

25 Pouches of 2 Caplets Each